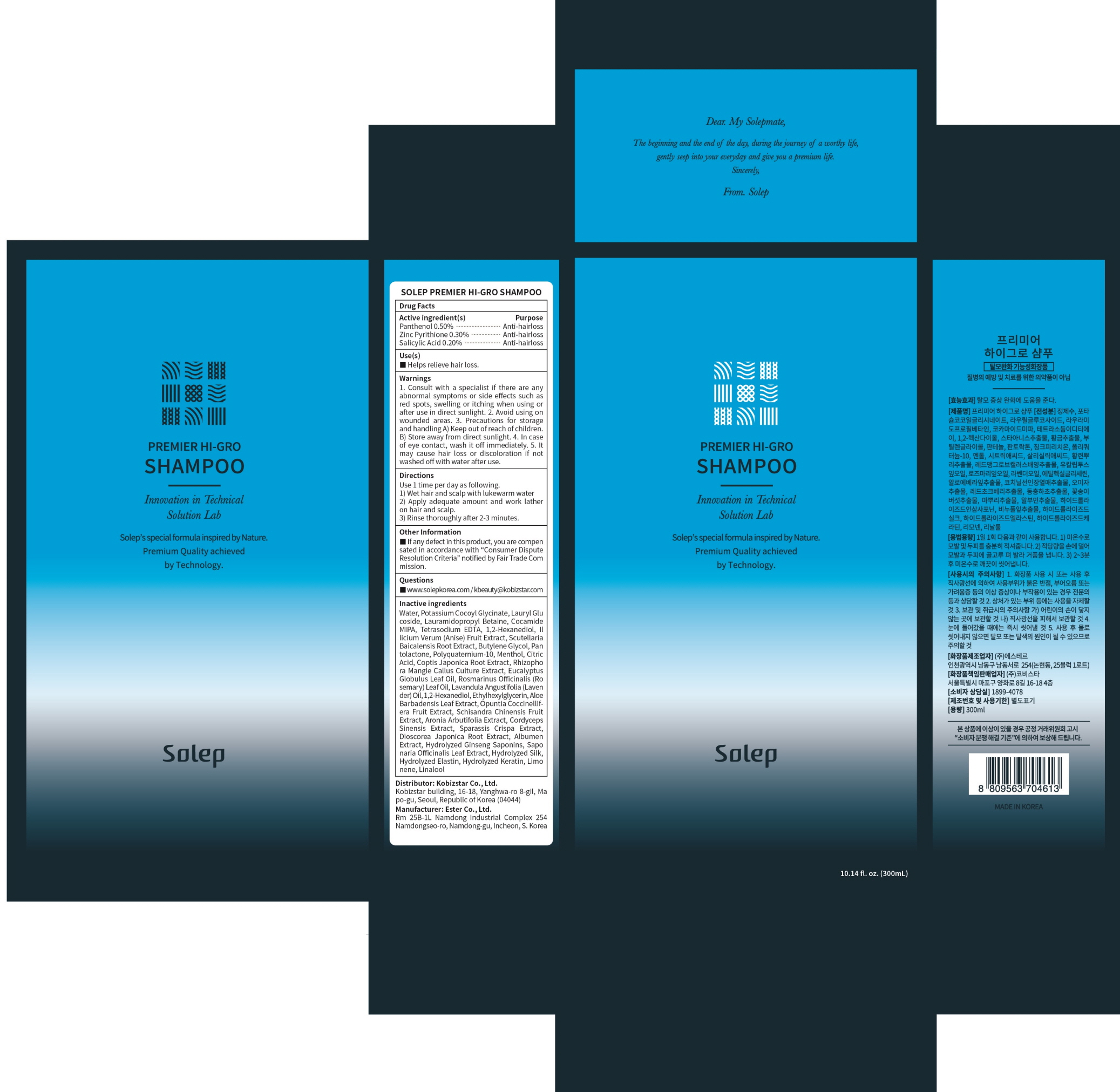 DRUG LABEL: SOLEP PREMIER HI GRO
NDC: 81077-010 | Form: SHAMPOO
Manufacturer: Kobizstar Co., Ltd.
Category: otc | Type: HUMAN OTC DRUG LABEL
Date: 20201117

ACTIVE INGREDIENTS: Panthenol 1.50 g/300 mL; PYRITHIONE ZINC 0.90 g/300 mL; Salicylic Acid 0.60 g/300 mL
INACTIVE INGREDIENTS: Water; Potassium Cocoyl Glycinate

ACTIVE INGREDIENT(S)

Panthenol 0.50%
Zinc Pyrithione 0.30%
Salicylic Acid 0.20%

INACTIVE INGREDIENTS

Water, Potassium Cocoyl Glycinate, Lauryl Glucoside, Lauramidopropyl Betaine, Cocamide MIPA, Tetrasodium EDTA, 1,2-Hexanediol, Illicium Verum (Anise) Fruit Extract, Scutellaria Baicalensis Root Extract, Butylene Glycol, Pantolactone, Polyquaternium-10, Menthol, Citric Acid, Coptis Japonica Root Extract, Rhizophora Mangle Callus Culture Extract, Eucalyptus Globulus Leaf Oil, Rosmarinus Officinalis (Rosemary) Leaf Oil, Lavandula Angustifolia (Lavender) Oil, 1,2-Hexanediol, Ethylhexylglycerin, Aloe Barbadensis Leaf Extract, Opuntia Coccinellifera Fruit Extract, Schisandra Chinensis Fruit Extract, Aronia Arbutifolia Extract, Cordyceps Sinensis Extract, Sparassis Crispa Extract, Dioscorea Japonica Root Extract, Albumen Extract, Hydrolyzed Ginseng Saponins, Saponaria Officinalis Leaf Extract, Hydrolyzed Silk, Hydrolyzed Elastin, Hydrolyzed Keratin, Limonene, Linalool

PURPOSE

Anti-hairloss

WARNINGS

1. Consult with a specialist if there are any abnormal symptoms or side effects such as red spots, swelling or itching when using or after use in direct sunlight. 2. Avoid using on wounded areas. 3. Precautions for storage and handling A) Keep out of reach of children. B) Store away from direct sunlight. 4. In case of eye contact, wash it off immediately. 5. It may cause hair loss or discoloration if not washed off with water after use.

KEEP OUT OF REACH OF CHILDREN

Use(s)

■ Helps relieve hair loss.

Directions

Use 1 time per day as following.
1) Wet hair and scalp with lukewarm water
2) Apply adequate amount and work lather on hair and scalp.
3) Rinse thoroughly after 2-3 minutes.

Other Information

■ If any defect in this product, you are compensated in accordance with “Consumer Dispute Resolution Criteria” notified by Fair Trade Commission.

Questions

■ www.solepkorea.com / kbeauty@kobizstar.com